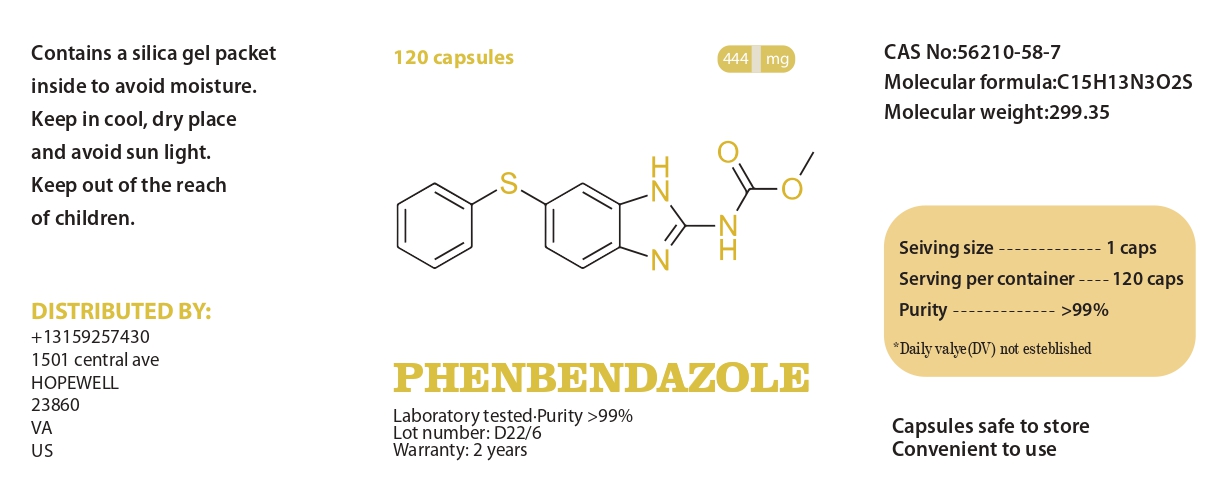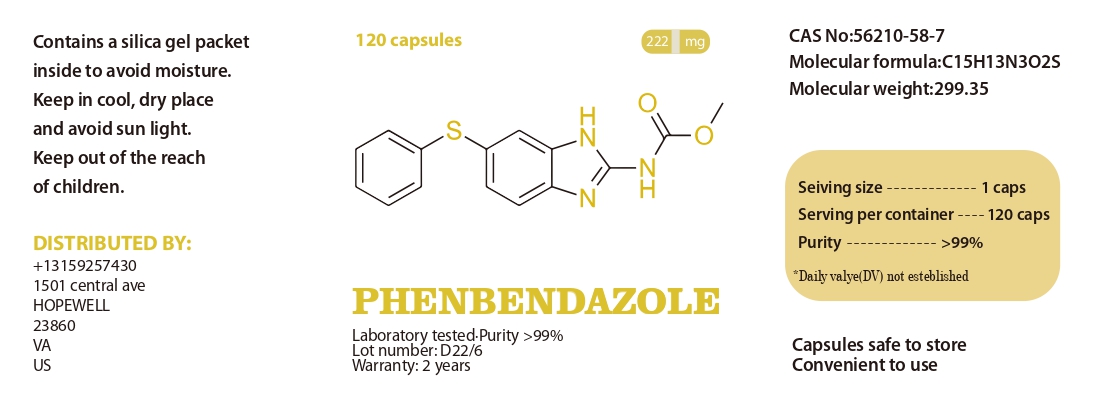 DRUG LABEL: PHENBENDAZOLE
NDC: 86202-3108 | Form: TABLET
Manufacturer: AMBIENCE FAMILY INC
Category: animal | Type: OTC ANIMAL DRUG LABEL
Date: 20240619

ACTIVE INGREDIENTS: fenbendazole 219 g/222 g

PHENBENDAZOLE

WARNINGS AND PRECAUTIONS

Contains a silica gel packet inside to avoid moisture.
Keep in cool, dry place and avoid sun light.
Keep out of the reach of children.

PHENBENDAZOLE

WARNINGS AND PRECAUTIONS

Not for use in humans. Keep out of reach of children. Protective gloves should be used and care should be taken when handling the product to avoid skin and eye exposure and accidental ingestion. Accidental exposure may result in skin and eye irritation. Accidental ingestion may cause gastrointestinal disturbances and hypersensitivity reactions in humans.

Capsules safe to store

Convenient to use

Laboratory tested·Purity >99%

Lot number: D22/6

Warranty: 2 years

Laboratory tested·Purity >99%
444 mg 120 capsules
CAS No:43210-67-9
Molecular formula:C15H13N3O2S
Molecular weight:299.35
Structural formula:
Contains: >99% fenbendazole
Lot number: F19/1-05
Warranty: 2 years
Contains a silica gel packet
inside to avoid moisture.
Keep in cool, dry place
and avoid sun light.
Keep out of the reach
of children.
DISTRIBUTED BY:
Hopaner Crest INC
United States
3717 Metro pkwy
Unit 3108
FL FORT MYERS
33916
Warranty: 2 years
Lot number: D22/6
PHENBENDAZOLE
Laboratory tested·Purity >99%
CAS No:56210-58-7
Molecular formula:C15H13N3O2S
Molecular weight:299.35
Contains a silica gel packet inside to avoid moisture.
Keep in cool, dry place and avoid sun light.
Keep out of the reach Capsules safe to store
Convenient to use Seiving size Serving per container
Purity
*Daily valye(DV) not esteblished
-------------
-------------
----120 caps
1 caps
99%
+13159257430
1501 central ave
HOPEWELL
23860
VA
US

PACKAGE LABEL

Laboratory tested·Purity >99%

444 mg 120 capsules
CAS No:43210-67-9
Molecular formula:C15H13N3O2S
Molecular weight:299.35
Structural formula:
Contains: >99% fenbendazole
Lot number: F19/1-05
Warranty: 2 years
Contains a silica gel packetinside to avoid moisture.

Keep in cool, dry place

and avoid sun light.
Keep out of the reach
of children.
DISTRIBUTED BY:
Hopaner Crest INC
United States
3717 Metro pkwy
Unit 3108
FL FORT MYERS
33916
Warranty: 2 years
Lot number: D22/6
PHENBENDAZOLE
Laboratory tested·Purity >99%
CAS No:56210-58-7
Molecular formula:C15H13N3O2S
Molecular weight:299.35
Contains a silica gel packet inside to avoid moisture.
Keep in cool, dry place and avoid sun light.
Keep out of the reach Capsules safe to store
Convenient to use Seiving size Serving per container
Purity
*Daily valye(DV) not esteblished
-------------
-------------
----120 caps
1 caps
99%
+13159257430
1501 central ave
HOPEWELL
23860
VA
US